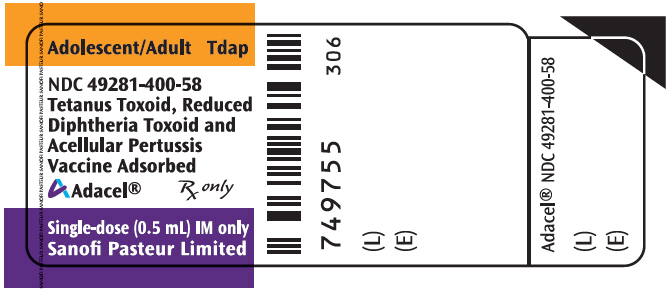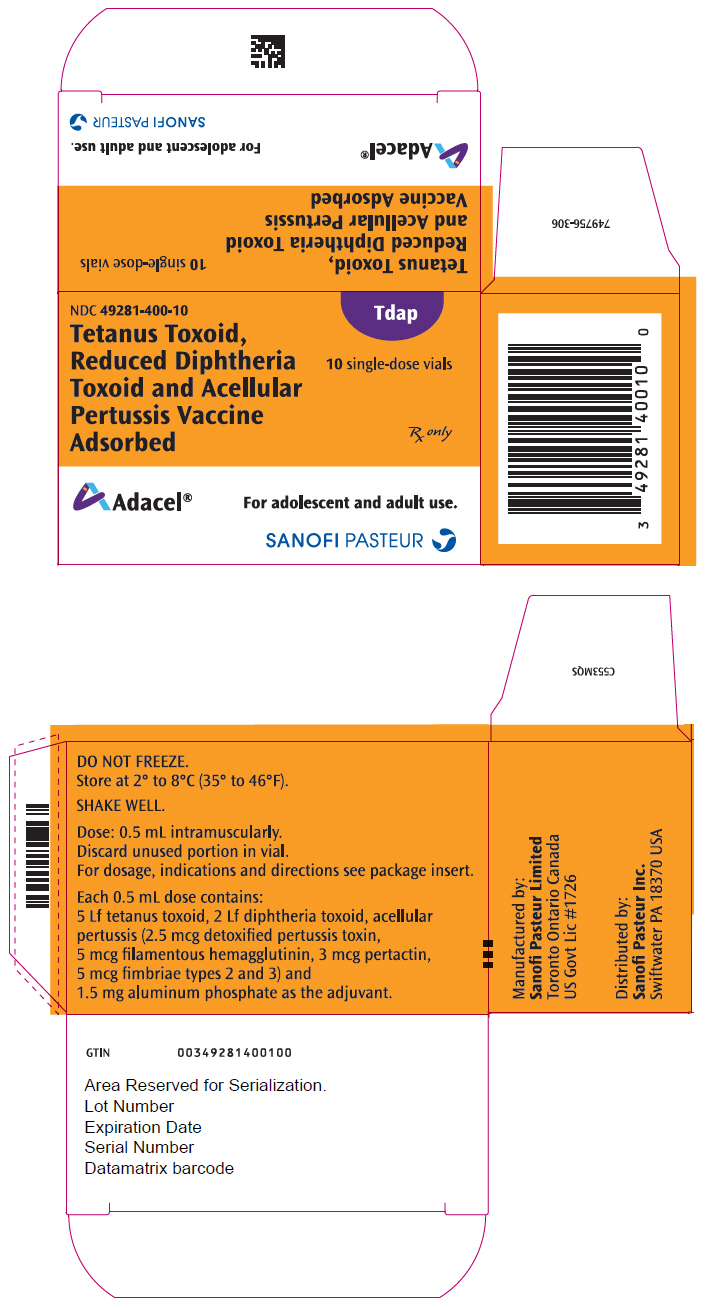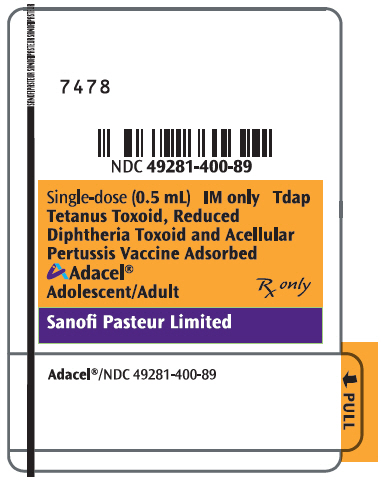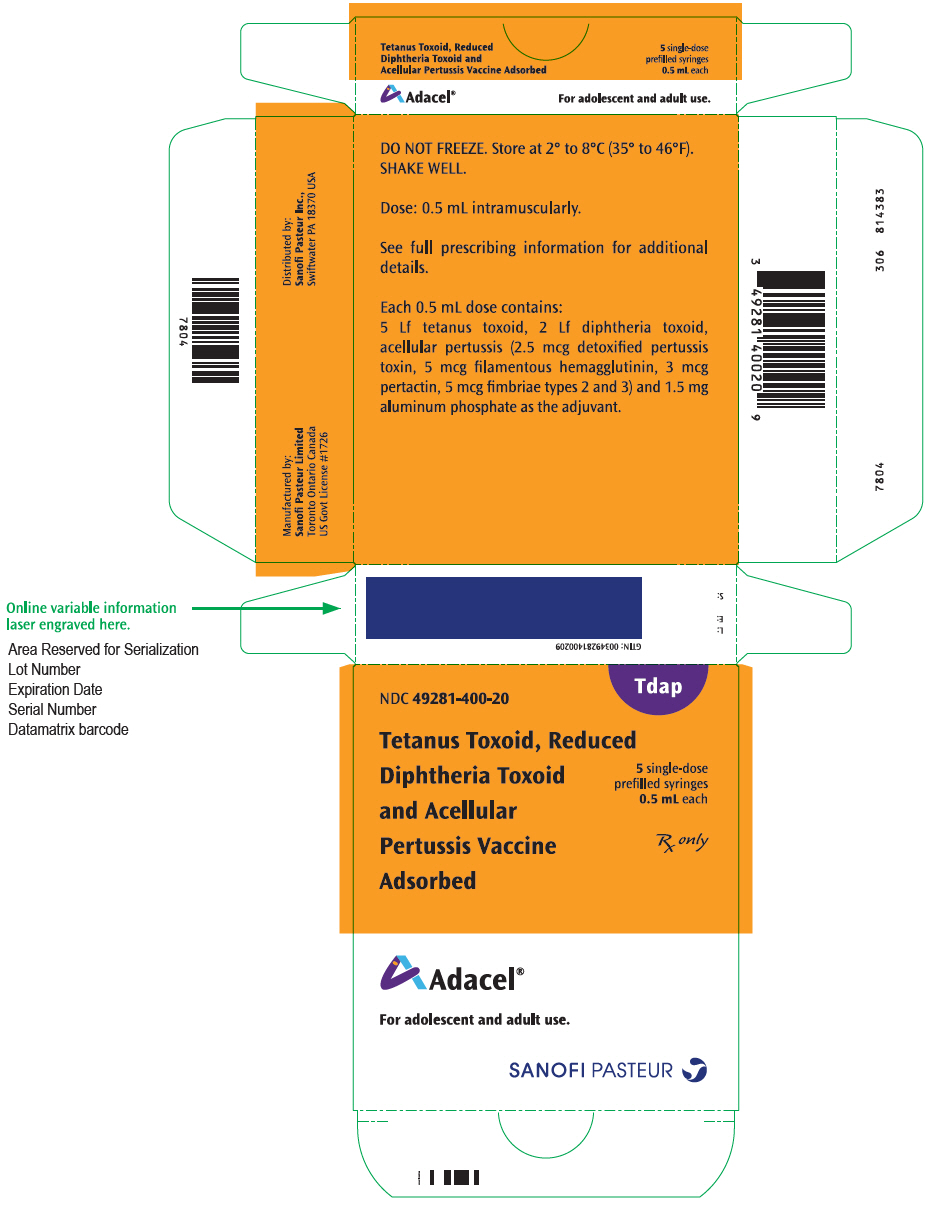 DRUG LABEL: Adacel
NDC: 49281-400 | Form: INJECTION, SUSPENSION
Manufacturer: Sanofi Pasteur Inc.
Category: other | Type: VACCINE LABEL
Date: 20240702

ACTIVE INGREDIENTS: CLOSTRIDIUM TETANI TOXOID ANTIGEN (FORMALDEHYDE INACTIVATED) 5 [Lf]/0.5 mL; CORYNEBACTERIUM DIPHTHERIAE TOXOID ANTIGEN (FORMALDEHYDE INACTIVATED) 2 [Lf]/0.5 mL; BORDETELLA PERTUSSIS TOXOID ANTIGEN (GLUTARALDEHYDE INACTIVATED) 2.5 ug/0.5 mL; BORDETELLA PERTUSSIS FILAMENTOUS HEMAGGLUTININ ANTIGEN (FORMALDEHYDE INACTIVATED) 5 ug/0.5 mL; BORDETELLA PERTUSSIS PERTACTIN ANTIGEN 3 ug/0.5 mL; BORDETELLA PERTUSSIS FIMBRIAE 2/3 ANTIGEN 5 ug/0.5 mL
INACTIVE INGREDIENTS: ALUMINUM PHOSPHATE 1.5 mg/0.5 mL; FORMALDEHYDE 5 ug/0.5 mL; GLUTARAL 50 ng/0.5 mL; PHENOXYETHANOL 3.3 mg/0.5 mL

HIGHLIGHTS OF PRESCRIBING INFORMATION

These highlights do not include all the information needed to use Adacel safely and effectively. See full prescribing information for Adacel.
Adacel (Tetanus Toxoid, Reduced Diphtheria Toxoid and Acellular Pertussis Vaccine Adsorbed), Suspension for Intramuscular Injection
Initial U.S. Approval: 2005

1 INDICATIONS AND USAGE

Adacel is a vaccine indicated for:

- active booster immunization against tetanus, diphtheria and pertussis. Adacel is approved for use in persons 10 through 64 years of age. (1)
- immunization during the third trimester of pregnancy to prevent pertussis in infants younger than 2 months of age. (1)

2 DOSAGE AND ADMINISTRATION

For intramuscular injection only.

- Each dose of Adacel is administered as a 0.5 mL injection. (2.1)
- For routine booster vaccination, a first dose of Adacel is administered 5 years or more after the last dose of Diphtheria and Tetanus Toxoids and Acellular Pertussis (DTaP) series or 5 years or more after vaccination with Tetanus and Diphtheria Toxoids Adsorbed (Td). A second dose of Adacel may be administered 8 years or more after the first dose with Tetanus Toxoid, Reduced Diphtheria Toxoid and Acellular Pertussis Vaccine Adsorbed (Tdap).
- Adacel may be administered for tetanus prophylaxis for wound management. For management of a tetanus prone wound, a booster dose of Adacel may be administered if at least 5 years have elapsed since previous receipt of a tetanus toxoid containing vaccine. (2.2)
- To provide protection against pertussis in infants younger than 2 months of age, administer Adacel during the third trimester of pregnancy

3 DOSAGE FORMS AND STRENGTHS

- Single-dose vials and prefilled syringes containing a 0.5 mL suspension for injection. (3)

4 CONTRAINDICATIONS

- Severe allergic reaction (e.g., anaphylaxis) to any component of Adacel or any other diphtheria toxoid, tetanus toxoid and pertussis antigen-containing vaccine. (4.1)
- Encephalopathy (e.g., coma, decreased level of consciousness, prolonged seizures) within 7 days of administration of a previous pertussis antigen-containing vaccine. (4.2)

5 WARNINGS AND PRECAUTIONS

- If Guillain-Barré syndrome occurred within 6 weeks of receipt of a prior vaccine containing tetanus toxoid, the risk for Guillain-Barré syndrome may be increased following a subsequent dose of Adacel vaccine. (5.3)
- Progressive or unstable neurologic conditions are reasons to defer Adacel vaccination. (5.4)
- Persons who experienced an Arthus-type hypersensitivity reaction following a prior dose of a tetanus toxoid-containing vaccine should not receive Adacel unless at least 10 years have elapsed since the last dose of a tetanus toxoid-containing vaccine. (5.5)
- Syncope (fainting) can occur in association with administration of injectable vaccines, including Adacel. Procedures should be in place to prevent falling injury and manage syncopal reactions. (5.7)

6 ADVERSE REACTIONS

- Following the first vaccination with Adacel, the most common solicited adverse reactions within 0-14 days of vaccination for Adolescents (11-17 years of age)/Adults (18-64 years of age) were:
  injection site pain (77.8%/65.7%), headache (43.7%/33.9%), body ache or muscle weakness (30.4%/21.9%), tiredness (30.2%/24.3%), injection site swelling (20.9%/21.0%), and injection site erythema (20.8%/24.7%). (6.1)
- Following a second vaccination with Adacel, the most common solicited reactions occurring within 0-7 days of vaccination for Adults (18-64 years of age) were:
  injection site pain (87.1%), myalgia (58.1%), headache (41.4%), malaise (33.3%), injection site swelling (6.9%), and injection site erythema (6.4%). (6.1)

To report SUSPECTED ADVERSE REACTIONS, contact Pharmacovigilance Department, Sanofi Pasteur Inc., Discovery Drive, Swiftwater, PA 18370 at 1-800-822-2463 (1-800-VACCINE) or VAERS at 1-800-822-7967 or http://vaers.hhs.gov.

7 DRUG INTERACTIONS

- When Adacel was administered concomitantly with trivalent inactivated influenza vaccine (TIV) to adults 19-64 years of age, a lower antibody response was observed for pertactin antigen as compared to Adacel administered alone. (7.1, 14.4)
- Immunosuppressive therapies may reduce the immune response to Adacel. (7.2)
- Do not mix Adacel with any other vaccine in the same syringe or vial.

8 USE IN SPECIFIC POPULATIONS

- Pregnancy Exposure Registry: contact Sanofi Pasteur Inc. at 1-800-822-2463 (1-800-VACCINE). (8.1)

FULL PRESCRIBING INFORMATION

1 INDICATIONS AND USAGE

Adacel® is a vaccine indicated for:

- Active booster immunization against tetanus, diphtheria and pertussis. Adacel is approved for use in individuals 10 through 64 years of age.

Immunization during the third trimester of pregnancy to prevent pertussis in infants younger than 2 months of age.

2 DOSAGE AND ADMINISTRATION

For intramuscular injection only.

2.1 Preparation for Administration

Just before use, shake the vial or syringe well until a uniform, white, cloudy suspension results.

Parenteral drug products should be inspected visually for particulate matter and discoloration prior to administration, whenever solution and container permit. If either of these conditions exist, the vaccine should not be administered.

Withdraw the 0.5 mL dose of vaccine from the single-dose vial using a sterile needle and syringe.

Adacel should not be combined through reconstitution or mixed with any other vaccine. Discard unused portion in vial.

2.2 Administration, Dose and Schedule

Adacel is administered as a single 0.5 mL intramuscular injection.

Routine Booster Vaccination

A first dose of Adacel is administered 5 years or more after the last dose of the Diphtheria and Tetanus Toxoids and Acellular Pertussis (DTaP) series or 5 years or more after a dose of Tetanus and Diphtheria Toxoids Adsorbed (Td). A second dose of Adacel may be administered 8 years or more after the first dose of Tetanus Toxoid, Reduced Diphtheria Toxoid and Acellular Pertussis Vaccine Adsorbed (Tdap).

Vaccination During the Third Trimester of Pregnancy

To prevent pertussis in infants younger than 2 months of age, administer Adacel to pregnant individuals during the third trimester of pregnancy.

Wound Management

Adacel may be administered for tetanus prophylaxis for wound management. For management of a tetanus prone wound, a booster dose of Adacel may be administered if at least 5 years have elapsed since previous receipt of a tetanus toxoid containing vaccine.

3 DOSAGE FORMS AND STRENGTHS

Adacel is a suspension for injection available in 0.5 mL single-dose vials and prefilled syringes. [See HOW SUPPLIED/STORAGE AND HANDLING (16).]

4 CONTRAINDICATIONS

4.1 Hypersensitivity

A severe allergic reaction (e.g., anaphylaxis) after a previous dose of any tetanus toxoid, diphtheria toxoid or pertussis containing vaccine or any other component of this vaccine is a contraindication to administration of Adacel. [See DESCRIPTION (11).] Because of uncertainty as to which component of the vaccine may be responsible, none of the components should be administered. Alternatively, such individuals may be referred to an allergist for evaluation if further immunizations are to be considered.

4.2 Encephalopathy

Encephalopathy (e.g., coma, prolonged seizures, or decreased level of consciousness) within 7 days of a previous dose of a pertussis containing vaccine not attributable to another identifiable cause is a contraindication to administration of any pertussis containing vaccine, including Adacel.

5 WARNINGS AND PRECAUTIONS

5.1 Management of Acute Allergic Reactions

Epinephrine hydrochloride solution (1:1,000) and other appropriate agents and equipment must be available for immediate use in case an anaphylactic or acute hypersensitivity reaction occurs.

5.2 Guillain-Barré Syndrome and Brachial Neuritis

If Guillain-Barré syndrome occurred within 6 weeks of receipt of prior vaccine containing tetanus toxoid, the risk for Guillain-Barré syndrome may be increased following a dose of Adacel. A review by the Institute of Medicine found evidence for acceptance of a causal relation between tetanus toxoid and brachial neuritis. (1)

5.3 Progressive or Unstable Neurologic Disorders

Progressive or unstable neurologic conditions are reasons to defer Adacel. It is not known whether administration of Adacel to persons with an unstable or progressive neurologic disorder might hasten manifestations of the disorder or affect the prognosis. Administration of Adacel to persons with an unstable or progressive neurologic disorder may result in diagnostic confusion between manifestations of the underlying illness and possible adverse effects of vaccination.

5.4 Arthus-Type Hypersensitivity

Persons who experienced an Arthus-type hypersensitivity reaction following a prior dose of a tetanus toxoid-containing vaccine should not receive Adacel unless at least 10 years have elapsed since the last dose of a tetanus toxoid containing vaccine.

5.5 Altered Immunocompetence

If Adacel is administered to immunocompromised persons, including persons receiving immunosuppressive therapy, the expected immune response may not be obtained. [See DRUG INTERACTIONS (7.2).]

5.6 Syncope

Syncope (fainting) can occur in association with administration of injectable vaccine, including Adacel. Procedures should be in place to prevent falling injury and manage syncopal reactions.

6 ADVERSE REACTIONS

6.1 Clinical Trials Experience

Because clinical trials are conducted under widely varying conditions, adverse reaction rates observed in the clinical trials of a vaccine cannot be directly compared to rates in the clinical trials of another vaccine and may not reflect the rates observed in practice. The adverse reaction information from clinical trials does, however, provide a basis for identifying the adverse events that appear to be related to vaccine use and for approximating rates of those events. As with any vaccine, there is the possibility that broad use of Adacel could reveal adverse reactions not observed in clinical trials.

The safety of a first vaccination with Adacel was evaluated in 5 clinical studies. Three of the studies were conducted in the U.S. and 2 were conducted in Canada. Of the study participants, 86% were Caucasian, 8% Black, 3% Hispanic, 1% Asian and 2% of other ethnic origin. A total of 7,143 individuals 10 through 64 years of age inclusive (4,695 adolescents 10 through 17 years of age and 2,448 adults 18 through 64 years of age) received a single dose of Adacel.

U.S. Adolescent and Adult Study of a First Vaccination with Adacel (Td506)

Clinical study Td506 was a randomized, observer-blind, active-controlled trial that enrolled adolescents 11 through 17 years of age (Adacel N = 1,184; DECAVAC (Tetanus and Diphtheria Toxoids Adsorbed; manufactured by Sanofi Pasteur Inc., Swiftwater, PA) N = 792) and adults 18 through 64 years of age (Adacel N = 1,752; DECAVAC N = 573). Study participants had not received tetanus or diphtheria-containing vaccines within the previous 5 years. Solicited local and systemic reactions and unsolicited adverse events were monitored daily for 14 days post vaccination using a diary card. From days 14 to 28 post vaccination, information on adverse events necessitating a medical contact, such as a telephone call, visit to an emergency room, physician's office or hospitalization, was obtained via telephone interview or at an interim clinic visit. From days 28 to 6 months post vaccination, participants were monitored for unexpected visits to a physician's office or to an emergency room, onset of serious illness, and hospitalizations. Information regarding adverse events that occurred in the 6-month post vaccination time period was obtained from participants via telephone contact. At least 96% of participants completed the 6-month follow-up evaluation.

The frequency of selected solicited adverse reactions (erythema, swelling, pain and fever) occurring during days 0 to 14 following vaccination with Adacel or Td vaccine in adolescents 11 through 17 years of age and adults 18 through 64 years of age are presented in Table 1. Most of these reactions were reported at a similar frequency in recipients of both Adacel and Td vaccine. Pain at the injection site was the most common adverse reaction in 62.9% to 77.8% of all vaccinees. In addition, overall rates of pain were higher in adolescent recipients of Adacel compared to Td vaccine recipients. Rates of moderate and severe pain in adolescents did not significantly differ between the Adacel and Td vaccine groups. Among adults, the rates of pain after receipt of Adacel or Td vaccine did not significantly differ. Fever of 38°C and higher was uncommon, although in the adolescent age group it occurred significantly more frequently in Adacel recipients than Td vaccine recipients.

Table 1: Frequencies of Solicited Injection Site Reactions and Fever for Adolescents and Adults, Days 0-14, Following a First Vaccination with Adacel or Td Vaccine in Study Td506
Adverse Reactions [The study sample size was designed to detect >10% differences between Adacel and Td vaccines for events of 'Any' intensity.]
Adverse Reactions [The study sample size was designed to detect >10% differences between Adacel and Td vaccines for events of 'Any' intensity.] |  | Adolescents 11-17 years Adacel N [N = number of participants with available data.] = 1,170-1,175 (%) | Adolescents 11-17 years Td [Tetanus and Diphtheria Toxoids Adsorbed manufactured by Sanofi Pasteur Inc., Swiftwater, PA.] N = 783-787 (%) | Adults 18-64 years Adacel N = 1,688-1,698 (%) | Adults 18-64 years Td N = 551-561 (%)
Injection Site Pain, Any |  | 77.8 [Adacel did not meet the non-inferiority criterion for rates of 'Any' Pain in adolescents compared to Td vaccine rates (upper limit of the 95% CI on the difference for Adacel minus Td vaccine was 10.7% whereas the criterion was <10%). For 'Any' Fever the non-inferiority criteria was met, however, 'Any' Fever was statistically higher in adolescents receiving Adacel.] | 71.0 | 65.7 | 62.9
Injection Site Pain, Moderate [Interfered with activities, but did not necessitate medical care or absenteeism.] |  | 18.0 | 15.6 | 15.1 | 10.2
Injection Site Pain, Severe [Incapacitating, prevented the performance of usual activities, may have/or did necessitate medical care or absenteeism.] |  | 1.5 | 0.6 | 1.1 | 0.9
Injection Site Swelling, Any |  | 20.9 | 18.3 | 21.0 | 17.3
Injection Site Swelling, Moderate 1.0 to 3.4 cm |  | 6.5 | 5.7 | 7.6 | 5.4
Injection Site Swelling, Severe ≥3.5 cm |  | 6.4 | 5.5 | 5.8 | 5.5
Injection Site Swelling, Severe ≥5 cm (2 inches) |  | 2.8 | 3.6 | 3.2 | 2.7
Injection Site Swelling, Any |  | 20.8 | 19.7 | 24.7 | 21.6
Injection Site Swelling, Moderate 1.0 to 3.4 cm |  | 5.9 | 4.6 | 8.0 | 8.4
Injection Site Swelling, Severe≥3.5 cm |  | 6.0 | 5.3 | 6.2 | 4.8
Injection Site Swelling, Severe≥5 cm (2 inches) |  | 2.7 | 2.9 | 4.0 | 3.0
Fever, ≥38.0°C (≥100.4°F) |  | 5.0 | 2.7 | 1.4 | 1.1
Fever, ≥38.8°C to ≤39.4°C (≥102.0°F to ≤103.0°F) |  | 0.9 | 0.6 | 0.4 | 0.2
Fever, ≥39.5°C (≥103.1°F) |  | 0.2 | 0.1 | 0.0 | 0.2

The frequency of other solicited adverse reactions (days 0-14) are presented in Table 2. The rates of these reactions following a first vaccination with Adacel were comparable with those observed with Td vaccine. Headache was the most frequent systemic reaction and was usually of mild to moderate intensity.

Table 2: Frequencies of Other Solicited Adverse Reactions for Adolescents and Adults, Days 0-14, Following a First Vaccination with Adacel or Td Vaccine in Study Td506
Adverse Reaction
Adverse Reaction |  | Adolescents 11-17 years Adacel N [N = number of participants with available data.] = 1,174-1,175 (%) | Adolescents 11-17 years Td [Tetanus and Diphtheria Toxoids Adsorbed manufactured by Sanofi Pasteur Inc., Swiftwater, PA.] N = 787 (%) | Adults 18-64 years Adacel N = 1,697-1,698 (%) | Adults 18-64 years Td N = 560-561 (%)
Headache, Any |  | 43.7 | 40.4 | 33.9 | 34.1
Headache, Moderate [Interfered with activities, but did not necessitate medical care or absenteeism.] |  | 14.2 | 11.1 | 11.4 | 10.5
Headache, Severe [Incapacitating, prevented the performance of usual activities, may have/or did necessitate medical care or absenteeism.] |  | 2.0 | 1.5 | 2.8 | 2.1
Body Ache or Muscle Weakness, Any |  | 30.4 | 29.9 | 21.9 | 18.8
Body Ache or Muscle Weakness, Moderate |  | 8.5 | 6.9 | 6.1 | 5.7
Body Ache or Muscle Weakness, Severe |  | 1.3 | 0.9 | 1.2 | 0.9
Tiredness, Any |  | 30.2 | 27.3 | 24.3 | 20.7
Tiredness, Moderate |  | 9.8 | 7.5 | 6.9 | 6.1
Tiredness, Severe |  | 1.2 | 1.0 | 1.3 | 0.5
Chills, Any |  | 15.1 | 12.6 | 8.1 | 6.6
Chills, Moderate |  | 3.2 | 2.5 | 1.3 | 1.6
Chills, Severe |  | 0.5 | 0.1 | 0.7 | 0.5
Sore and Swollen Joints, Any |  | 11.3 | 11.7 | 9.1 | 7.0
Sore and Swollen Joints, Moderate |  | 2.6 | 2.5 | 2.5 | 2.1
Sore and Swollen Joints, Severe |  | 0.3 | 0.1 | 0.5 | 0.5
Nausea, Any |  | 13.3 | 12.3 | 9.2 | 7.9
Nausea, Moderate |  | 3.2 | 3.2 | 2.5 | 1.8
Nausea, Severe |  | 1.0 | 0.6 | 0.8 | 0.5
Lymph Node Swelling, Any |  | 6.6 | 5.3 | 6.5 | 4.1
Lymph Node Swelling, Moderate |  | 1.0 | 0.5 | 1.2 | 0.5
Lymph Node Swelling, Severe |  | 0.1 | 0.0 | 0.1 | 0.0
Diarrhea, Any |  | 10.3 | 10.2 | 10.3 | 11.3
Diarrhea, Moderate |  | 1.9 | 2.0 | 2.2 | 2.7
Diarrhea, Severe |  | 0.3 | 0.0 | 0.5 | 0.5
Vomiting, Any |  | 4.6 | 2.8 | 3.0 | 1.8
Vomiting, Moderate |  | 1.2 | 1.1 | 1.0 | 0.9
Vomiting, Severe |  | 0.5 | 0.3 | 0.5 | 0.2
Rash, Any |  | 2.7 | 2.0 | 2.0 | 2.3

Injection site and systemic solicited reactions occurred at similar rates in Adacel and Td vaccine recipients in the 3 day post-vaccination period. Most injection site reactions occurred within the first 3 days after vaccination (with a mean duration of less than 3 days). The rates of unsolicited adverse events reported from days 14-28 post-vaccination were comparable between the two vaccine groups, as were the rates of unsolicited adverse events from day 28 through 6 months. There were no spontaneous reports of extensive limb swelling of the injected limb in study Td506, nor in the other three studies which also contributed to the safety database for Adacel.

Adult Study of a Second Vaccination with Adacel (NCT01439165)

In a randomized, observer-blind, active-controlled, multi-center study (NCT01439165), adults 18 through 64 years of age who had received a first dose of Adacel 8-12 years previously were enrolled and randomized to receive either Adacel (N = 1002) or a US licensed Td vaccine, TENIVAC (Tetanus and Diphtheria Toxoids Adsorbed; manufactured by Sanofi Pasteur, Limited) (N = 328). Subjects were recruited from the primary licensure study Td506 and the Canadian general public and had not received Td or Tdap vaccine since their initial Adacel dose. The demographic characteristics for study participants were similar for both vaccine groups. The mean ages were 28.9 years for the Adacel group and 29.2 years for the Td group. Overall, there were more female participants in both the Adacel group and Td group; 64.5% and 64.6%, respectively. In both vaccine groups, greater than 94% of subjects identified as white and 99% as non-Hispanic or Latino.

Safety data were collected from all participants who received the study vaccine (N = 999 for the Adacel group; N = 328 for the Td group). Solicited local and systemic reactions and unsolicited adverse events were monitored for 7 days post-vaccination using a diary card. Unsolicited adverse events were collected for approximately 28 days post-vaccination. Serious adverse events were collected throughout the study period (up to 6 months post-vaccination).

Solicited adverse reactions reported to occur during days 0-7 following vaccination are presented in Table 3.

Table 3: Frequencies of Solicited Adverse Reactions 0-7 Days Following a Second Vaccination with Adacel Compared to Td Vaccine in Study NCT01439165 - Safety Analysis Set
Adverse Reaction |  | Adacel (N=999) (%) | Td Adsorbed [Tetanus and Diphtheria Toxoids Adsorbed manufactured by Sanofi Pasteur Limited, Toronto, Ontario, Canada.] (N=328) (%)
Injection site pain, Any |  | 87.1 | 87.4
Injection site pain, Grade 2 [Some interference with activity] |  | 28.5 | 31.4
Injection site pain, Grade 3 [Significant; prevents daily activity] |  | 3.6 | 2.8
Injection site erythema, Any |  | 6.4 | 5.5
Injection site erythema, Grade 2 (≥51 to ≤100 mm) |  | 2.1 | 2.8
Injection site erythema, Grade 3 (˃100 mm) |  | 0.2 | 0.0
Injection site swelling, Any |  | 6.9 | 8.0
Injection site swelling, Grade 2 (≥51 to ≤100 mm) |  | 2.4 | 2.2
Injection site swelling, Grade 3 (˃100 mm) |  | 0.3 | 0.0
Fever, Any |  | 0.9 | 1.8
Fever, Grade 2 (≥38.5°C to ≤38.9°C or ≥101.2°F to ≤102.0°F |  | 0.3 | 0.6
Fever, Grade 3 (≥102.1°F) |  | 0.2 | 0.3
Headache, Any |  | 41.4 | 39.1
Headache, Grade 2 |  | 12.4 | 10.5
Headache, Grade 3 |  | 2.6 | 4.0
Malaise, Any |  | 33.3 | 30.8
Malaise, Grade 2 |  | 9.3 | 9.8
Malaise, Grade 3 |  | 3.0 | 3.7
Myalgia, Any |  | 58.1 | 58.2
Myalgia, Grade 2 |  | 18.7 | 16.9
Myalgia, Grade 3 |  | 3.0 | 3.1
N = number of participants with available data

Adult Study of a Second Vaccination with Adacel (NCT00347958)

Study NCT00347958 was a descriptive, open-label, post-marketing, multi-center study evaluating the safety of Adacel readministration in adults 5 years following a previous dose of Adacel. The mean age of subjects was 31.7 years, there were more females (52.2%) than males (47.8%) and 89.9% of subjects were Caucasian. Solicited adverse reactions were collected for 14 days following vaccination. SAEs were monitored for 6 months following vaccination. A total of 545 subjects 16-69 years of age were enrolled. All participants in this study received a first dose of Adacel vaccine as part of Sanofi Pasteur studies Td501, Td502, or Td505. Approximately 90% of the participants had at least one solicited injection site reaction. The most frequently reported injection site reactions were pain in 87.6% of subjects, followed by erythema/redness in 28.6%, and swelling in 25.6%. Approximately 77% of the participants had at least one solicited systemic reaction. The most frequently reported solicited systemic adverse reactions in subjects who received a second dose of Adacel were myalgia (61%), followed by headache (53.2%), malaise (38.2%), and fever (6.5%).

Injection Site and Systemic Reactions Following Adacel Given Concomitantly with Hepatitis B Vaccine

In the concomitant vaccination study with Adacel (first vaccination) and Hepatitis B vaccine [Recombivax HB] (Td501) [See CLINICAL STUDIES (14)], injection site and systemic adverse events were monitored daily for 14 days post-vaccination using a diary card. Injection site adverse events were only monitored at site/arm of Adacel administration. Unsolicited reactions (including immediate reactions, serious adverse events and events that elicited seeking medical attention) were collected at a clinic visit or via telephone interview for the duration of the trial, i.e., up to 6 months post-vaccination.

The rates reported for fever and injection site pain (at the Adacel administration site) were similar when Adacel and Hepatitis B vaccine were given concurrently or separately. However, the rates of injection site erythema (23.4% for concomitant vaccination and 21.4% for separate administration) and swelling (23.9% for concomitant vaccination and 17.9% for separate administration) at the Adacel administration site were increased when coadministered. Swollen and/or sore joints were reported by 22.5% for concomitant vaccination and 17.9% for separate administration. The rates of generalized body aches in the individuals who reported swollen and/or sore joints were 86.7% for concomitant vaccination and 72.2% for separate administration. Most joint complaints were mild in intensity with a mean duration of 1.8 days. The incidence of other solicited and unsolicited adverse events were not different between the 2 study groups.

Injection Site and Systemic Reactions Following Adacel Given Concomitantly with Trivalent Inactivated Influenza Vaccine (TIV)

In the concomitant vaccination study with Adacel (first vaccination) and trivalent inactivated influenza vaccine [Fluzone] (Td502) [See CLINICAL STUDIES (14)], injection site and systemic adverse events were monitored for 14 days post-vaccination using a diary card. All unsolicited reactions occurring through day 14 were collected. From day 14 to the end of the trial, i.e., up to 84 days, only events that elicited seeking medical attention were collected.

The rates of fever and injection site erythema and swelling were similar for recipients of concurrent and separate administration of Adacel and TIV. However, pain at the Adacel injection site occurred at statistically higher rates following concurrent administration (66.6%) versus separate administration (60.8%). The rates of sore and/or swollen joints were 13% for concurrent administration and 9% for separate administration. Most joint complaints were mild in intensity with a mean duration of 2.0 days. The incidence of other solicited and unsolicited adverse events was similar between the 2 study groups.

Additional Studies

In an additional study (Td505), 1,806 adolescents 11 through 17 years of age received Adacel (first vaccination) as part of the lot consistency study used to support Adacel licensure. This study was a randomized, double-blind, multi-center trial designed to assess lot consistency as measured by the safety and immunogenicity of 3 lots of Adacel when given as a booster dose to adolescents 11 through 17 years of age inclusive. Local and systemic adverse events were monitored for 14 days post-vaccination using a diary card. Unsolicited adverse events and serious adverse events were collected for 28 days post-vaccination. Pain was the most frequently reported local adverse event occurring in approximately 80% of all participants. Headache was the most frequently reported systemic event occurring in approximately 44% of all participants. Sore and/or swollen joints were reported by approximately 14% of participants. Most joint complaints were mild in intensity with a mean duration of 2.0 days.

An additional 962 adolescents and adults received Adacel in three supportive Canadian studies (TC9704, Td9707 and TD9805) used as the basis for licensure in other countries. Within these clinical trials, the rates of local and systemic reactions following the first vaccination with Adacel were similar to those reported in the four principal trials in the U.S. with the exception of a higher rate (86%) of adults experiencing "any" local injection site pain. The rate of severe pain (0.8%), however, was comparable to the rates reported in four principal trials conducted in the US. There was one spontaneous report of whole-arm swelling of the injected limb among the 277 Td vaccine recipients, and two spontaneous reports among the 962 Adacel recipients in the supportive Canadian studies.

An additional study (NCT01311557) enrolled 1,302 individuals in an open label, two-arm, multicenter trial (651 participants in each group) to evaluate the safety and immunogenicity of a first vaccination with Adacel administered to persons 10 to <11 years of age compared to persons 11 to <12 years of age. Immediate reactions were monitored for 20 minutes post-vaccination. Solicited local and systemic adverse events were monitored for 7 days post-vaccination using a diary card. Unsolicited and serious adverse events were collected for approximately 30 days post-vaccination. Similar rates of immediate, solicited and unsolicited adverse reactions were reported in each of the two age cohorts. One serious adverse event, not related to vaccination, was reported in the younger age group.

Serious Adverse Events

Throughout the 6-month follow-up period following a first vaccination with Adacel in study Td506, SAEs were reported in 1.5% of Adacel recipients and in 1.4% of Td vaccine recipients. Two SAEs in adults were neuropathic events that occurred within 28 days of Adacel administration; one severe migraine with unilateral facial paralysis and one diagnosis of nerve compression in neck and left arm. Similar or lower rates of serious adverse events were reported in the other trials following a first vaccination with Adacel in participants up to 64 years of age and no additional neuropathic events were reported.

In study NCT01439165 when a second vaccination of Adacel was administered 8-12 years following the initial vaccination of Adacel, a total of 8 participants (0.8%) in the Adacel group and 1 participant (0.3%) in the Td group reported SAEs during the 6-month follow-up period. All SAEs were considered by the investigator to be unrelated to the study vaccine.

In study NCT00347958, seven participants experienced an SAE, all of which were considered by the investigator to be unrelated to the study vaccine.

6.2 Postmarketing Experience

The following adverse events of Adacel have been spontaneously reported in the US and other countries. Because these events are reported voluntarily from a population of uncertain size, it may not be possible to reliably estimate their frequency or establish a causal relationship to vaccine exposure.

The following adverse events were included based on one or more of the following factors: severity, frequency of reporting, or strength of evidence for a causal relationship to Adacel.

- Immune system disorders
  Anaphylactic reaction, hypersensitivity reaction (angioedema, edema, rash, hypotension)
- Nervous system disorders
  Paresthesia, hypoesthesia, Guillain-Barré syndrome, brachial neuritis, facial palsy, convulsion, syncope, myelitis
- Cardiac disorders
  Myocarditis
- Skin and subcutaneous tissue disorders
  Pruritus, urticaria
- Musculoskeletal and connective tissue disorders
  Myositis, muscle spasm
- General disorders and administration site conditions
  Large injection site reactions (>50 mm), extensive limb swelling from the injection site beyond one or both joints
  Injection site bruising, injection site nodule, sterile abscess, Arthus hypersensitivity

7 DRUG INTERACTIONS

7.1 Concomitant Vaccine Administration

When Adacel is administered concomitantly with other injectable vaccines or Tetanus Immune Globulin, they should be given with separate syringes and at different injection sites. Adacel should not be mixed with any other vaccine in the same syringe or vial.

Trivalent Inactivated Influenza Vaccine (TIV)

In a clinical study Adacel (first vaccination) was administered concomitantly with a US-licensed trivalent inactivated influenza vaccine (TIV). [See ADVERSE REACTIONS (6.1) and CLINICAL STUDIES (14).]

No interference in tetanus and diphtheria seroprotection rates and responses to influenza vaccine, detoxified pertussis toxin (PT), fimbriae types 2 and 3 (FIM) or filamentous hemagglutinin (FHA) were observed when Adacel vaccine was administered concomitantly with TIV compared to separate administration. A lower pertactin (PRN) GMC was observed when Adacel was administered concomitantly with TIV compared to separate administration.

7.2 Immunosuppressive Treatments

Immunosuppressive therapies, including irradiation, antimetabolites, alkylating agents, cytotoxic drugs and corticosteroids (used in greater than physiologic doses), may reduce the immune response to vaccines. [See WARNINGS AND PRECAUTIONS (5.6).]

8 USE IN SPECIFIC POPULATIONS

8.1 Pregnancy

Pregnancy Exposure Registry

There is a pregnancy exposure registry that monitors pregnancy outcomes in women exposed to Adacel during pregnancy. Women who receive Adacel during pregnancy are encouraged to contact directly, or have their healthcare professional contact, Sanofi Pasteur Inc. at 1-800-822-2463 (1-800-VACCINE) or online at https://www.sanofipasteurpregnancyregistry.com.

Risk Summary

All pregnancies have a risk of birth defect, loss or other adverse outcomes. In the US general population, the estimated background risk of major birth defects and miscarriage in clinically recognized pregnancies is 2% to 4% and 15% to 20%, respectively.

Available data suggest the rates of major birth defects and miscarriage in women who receive Adacel within 30 days prior to pregnancy or during pregnancy are consistent with estimated background rates. (See Human Data)

Two developmental toxicity studies were performed in female rabbits given 0.5 mL (a single human dose) of Adacel twice prior and during gestation. The studies revealed no evidence of harm to the fetus due to Adacel. (See Animal Data)

Data

Human Data

A retrospective passive surveillance study (NCT00258882) included women who received Adacel during pregnancy (n=225) and controls (n=675) matched by age and date of first positive pregnancy test. Of the 225 Adacel recipients, 39 women received Adacel within two weeks prior to the date of their last menstrual period (LMP), 110 were vaccinated during the 1st trimester (< 12 weeks gestation), 33 during the 2nd trimester (12 to < 27 weeks gestation), 14 in 3rd trimester (11 from 27 to <36 weeks gestation and 3 from ≥36 weeks gestation), and 29 were unknown. There were 21 reports of spontaneous abortion (9.3%) and 15 congenital anomalies (6.7%) in the Adacel exposed group, and 102 spontaneous abortions (15%) and 57 congenital anomalies (8.4%) in the control group.

An assessment of data from the ongoing pregnancy registry included 1236 prospective reports of exposure to Adacel during pregnancy since 10 June 2005 through 16 October 2022. Among the 286 reports with known pregnancy outcomes, 118 women were exposed to Adacel in the first trimester with 1 congenital anomaly and 14 spontaneous abortions; 54 women were exposed to Adacel in the second trimester with one congenital anomaly; 114 women were exposed to Adacel in the third trimester with 2 congenital anomalies; 76 women were exposed to Adacel at an unknown trimester with 1 congenital anomaly. The rates of assessed outcomes in the prospective population were consistent with estimated background rates.

Animal Data

The effect of Adacel on embryo-fetal and pre-weaning development was evaluated in two developmental toxicity studies in female rabbits. Animals were administered 0.5 mL (a single human dose) of Adacel twice prior to gestation, during the period of organogenesis (gestation day 6) and later during pregnancy on gestation day 29. No adverse effects on pregnancy, parturition, lactation, embryo-fetal or pre-weaning development were observed. There were no vaccine related fetal malformations or other evidence of teratogenesis noted in this study.

8.2 Lactation

Risk Summary

It is not known whether Adacel vaccine components are excreted in human milk. Data are not available to assess the effect of administration of Adacel on breast-fed infants or on milk production/excretion.

The developmental and health benefits of breastfeeding should be considered along with the mother's clinical need for Adacel and any potential adverse effects on the breastfed child from Adacel or from the underlying maternal condition. For preventive vaccines, the underlying maternal condition is susceptibility to disease prevented by the vaccine.

8.4 Pediatric Use

Adacel is not approved for individuals less than 10 years of age. Safety and effectiveness of Adacel in persons less than 10 years of age in the U.S. have not been established.

8.5 Geriatric Use

Adacel is not approved for use in individuals 65 years of age and older.

In a clinical study, individuals 65 years of age and older received a single dose of Adacel. Based on prespecified criteria, persons 65 years of age and older who received a dose of Adacel had lower geometric mean concentrations of antibodies to PT, PRN and FIM when compared to infants who had received a primary series of DAPTACEL®, Diphtheria and Tetanus Toxoids and Acellular Pertussis Vaccine Adsorbed (DTaP). [See CLINICAL STUDIES (14) for description of DAPTACEL.]

11 DESCRIPTION

Adacel is a sterile isotonic suspension of tetanus and diphtheria toxoids and pertussis antigens adsorbed on aluminum phosphate, for intramuscular injection.

Each 0.5 mL dose contains 5 Lf tetanus toxoid (T), 2 Lf diphtheria toxoid (d), and acellular pertussis antigens [2.5 mcg detoxified pertussis toxin (PT), 5 mcg filamentous hemagglutinin (FHA), 3 mcg pertactin (PRN), 5 mcg fimbriae types 2 and 3 (FIM)]. Other ingredients per 0.5 mL dose include 1.5 mg aluminum phosphate (0.33 mg aluminum) as the adjuvant, ≤5 mcg residual formaldehyde, <50 ng residual glutaraldehyde and 3.3 mg (0.6% v/v) 2-phenoxyethanol (not as a preservative). The antigens are the same as those in DAPTACEL; however, Adacel is formulated with reduced quantities of diphtheria and detoxified PT.

The acellular pertussis vaccine components are produced from Bordetella pertussis cultures grown in Stainer-Scholte medium (2) modified by the addition of casamino acids and dimethyl-beta-cyclodextrin. PT, FHA and PRN are isolated separately from the supernatant culture medium. FIM are extracted and copurified from the bacterial cells. The pertussis antigens are purified by sequential filtration, salt-precipitation, ultrafiltration and chromatography. PT is detoxified with glutaraldehyde, FHA is treated with formaldehyde, and the residual aldehydes are removed by ultrafiltration. The individual antigens are adsorbed onto aluminum phosphate.

The tetanus toxin is produced from Clostridium tetani grown in modified Mueller-Miller casamino acid medium without beef heart infusion. (3) Tetanus toxin is detoxified with formaldehyde and purified by ammonium sulfate fractionation and diafiltration. Corynebacterium diphtheriae is grown in modified Mueller's growth medium. (4) After purification by ammonium sulfate fractionation, diphtheria toxin is detoxified with formaldehyde and diafiltered.

The adsorbed diphtheria, tetanus and acellular pertussis components are combined with aluminum phosphate (as adjuvant), 2-phenoxyethanol (not as a preservative) and water for injection. Adacel does not contain a preservative.

In the guinea pig potency test, the tetanus component induces at least 2 neutralizing units/mL of serum and the diphtheria component induces at least 0.5 neutralizing units/mL of serum. The potency of the acellular pertussis vaccine components is evaluated by the antibody response of immunized mice to detoxified PT, FHA, PRN and FIM as measured by enzyme-linked immunosorbent assay (ELISA).

Diphtheria and tetanus toxoids are individually adsorbed onto aluminum phosphate.

12 CLINICAL PHARMACOLOGY

12.1 Mechanism of Action

Tetanus

Tetanus is a disease manifested primarily by neuromuscular dysfunction caused by a potent exotoxin released by C tetani.

Protection against disease is due to the development of neutralizing antibodies to tetanus toxin. A serum tetanus antitoxin level of at least 0.01 IU/mL, measured by neutralization assay is considered the minimum protective level. (5) (6)

Diphtheria

Diphtheria is an acute toxin-mediated disease caused by toxigenic strains of C diphtheriae. Protection against disease is due to the development of neutralizing antibodies to diphtheria toxin. A serum diphtheria antitoxin level of 0.01 IU/mL is the lowest level giving some degree of protection. Antitoxin levels of at least 0.1 IU/mL are generally regarded as protective. (5) Levels of 1.0 IU/mL have been associated with long-term protection. (7)

Pertussis

Pertussis (whooping cough) is a respiratory disease caused by B pertussis. This Gram-negative coccobacillus produces a variety of biologically active components, though their role in either the pathogenesis of, or immunity to, pertussis has not been clearly defined.

13 NONCLINICAL TOXICOLOGY

13.1 Carcinogenesis, Mutagenesis, Impairment of Fertility

Adacel has not been evaluated for carcinogenic or mutagenic potential, or impairment of male fertility.

14 CLINICAL STUDIES

The effectiveness of the tetanus toxoid and diphtheria toxoid used in Adacel was based on the immune response to these antigens compared to a US licensed Tetanus and Diphtheria Toxoids Adsorbed For Adult Use (Td) vaccine manufactured by Sanofi Pasteur Inc., Swiftwater, PA. The primary measures for immune response to the diphtheria and tetanus toxoids were the percentage of participants attaining an antibody level of at least 0.1 IU/mL.

The effectiveness of the pertussis antigens used in Adacel was evaluated based on a comparison of pertussis antibody levels achieved in recipients of Adacel with those obtained in infants after three or four doses of DAPTACEL. For the first dose of Adacel, the comparisons were to infants who received three doses of DAPTACEL in the Sweden I Efficacy trial. For the second dose of Adacel, for the evaluation of FHA, PRN, and FIM antibody levels, the comparisons were to infants who received three doses of DAPTACEL in the Sweden I Efficacy trial; for evaluation of PT antibody levels, the comparison was to infants who received four doses of DAPTACEL in a US safety and immunogenicity study (Study NCT00255047). In the Sweden I Efficacy Trial, three doses of DAPTACEL vaccine were shown to confer a protective efficacy of 84.9% (95% CI: 80.1%, 88.6%) against WHO defined pertussis (21 days of paroxysmal cough with laboratory-confirmed B pertussis infection or epidemiological link to a confirmed case). The protective efficacy against mild pertussis (defined as at least one day of cough with laboratory-confirmed B pertussis infection) was 77.9% (95% CI: 72.6%, 82.2%). (8)

In addition, the ability of Adacel to elicit a booster response (defined as rise in antibody concentration after vaccination) to the tetanus, diphtheria and pertussis antigens following vaccination was evaluated.

14.1 Immunological Evaluation in Adolescents and Adults, 11 through 64 Years of Age Following a First Vaccination with Adacel (Td506)

Study Td506 was a comparative, multi-center, randomized, observer-blind, controlled trial which enrolled 4,480 participants; 2,053 adolescents (11-17 years of age) and 2,427 adults (18-64 years of age). Enrollment was stratified by age to ensure adequate representation across the entire age range. Participants had not received a tetanus or diphtheria toxoid containing vaccine within the previous 5 years. After enrollment participants were randomized to receive one dose of either Adacel or Td vaccine. A total of 4,461 randomized participants were vaccinated. The per-protocol immunogenicity subset included 1,270 Adacel recipients and 1,026 Td vaccine recipients. Sera were obtained before and approximately 35 days after vaccination. [Blinding procedures for safety assessments are described in ADVERSE REACTIONS (6).]

Demographic characteristics were similar within age groups and between the vaccine groups. A total of 76% of the adolescents and 1.1% of the adults reported a history of receiving 5 previous doses of diphtheria-tetanus-pertussis containing vaccines. Anti-tetanus and anti-diphtheria seroprotection rates (≥0.1 IU/mL) and booster response rates were comparable between Adacel and Td vaccines. (See Table 4 and Table 5.) Adacel induced pertussis antibody levels that were non-inferior to those of Swedish infants who received three doses of DAPTACEL vaccine (Sweden I Efficacy Study). (See Table 6.) Acceptable booster responses to each of the pertussis antigens were also demonstrated, i.e., the percentage of participants with a booster response exceeded the predefined lower limit. (See Table 7.)

Table 4: Pre-vaccination and Post-vaccination Antibody Responses and Booster Response Rates to Tetanus Toxoid Following a First Vaccination with Adacel Vaccine as Compared to Td Vaccine in Adolescents and Adults 11 through 64 Years of Age (Td506)
 |  |  | Anti-Tetanus toxoid (IU/mL) Pre-vaccination | Anti-Tetanus toxoid (IU/mL) Pre-vaccination | Anti-Tetanus toxoid (IU/mL) 1 Month Post-vaccination | Anti-Tetanus toxoid (IU/mL) 1 Month Post-vaccination | Anti-Tetanus toxoid (IU/mL) 1 Month Post-vaccination
Age Group (years) | Vaccine | N [N = number of participants in the per-protocol population with available data.] | % ≥0.10 (95% CI) | % ≥1.0 (95% CI) | % ≥0.10 (95% CI) | % ≥1.0 (95% CI) | % Booster [Booster response is defined as: A 4-fold rise in antibody concentration, if the pre-vaccination concentration was equal to or below the cut-off value and a 2-fold rise in antibody concentration if the pre-vaccination concentration was above the cut-off value. The cut-off value for tetanus was 2.7 IU/mL.] (95% CI)
11-17 | Adacel | 527 | 99.6 (98.6, 100.0) | 44.6 (40.3, 49.0) | 100.0 [Seroprotection rates at ≥0.10 IU/mL and booster response rates to Adacel were non-inferior to Td vaccine (upper limit of the 95% CI on the difference for Td vaccine minus Adacel <10%).] (99.3, 100.0) | 99.6 [Seroprotection rates at ≥1.0 IU/mL were not prospectively defined as a primary endpoint.] (98.6, 100.0) | 91.7 (89.0, 93.9)
11-17 | Td [Tetanus and Diphtheria Toxoids Adsorbed manufactured by Sanofi Pasteur Inc., Swiftwater, PA.] | 516 | 99.2 (98.0, 99.8) | 43.8 (39.5, 48.2) | 100.0 (99.3, 100.0) | 99.4 (98.3, 99.9) | 91.3 (88.5, 93.6)
18-64 | Adacel | 742-743 | 97.3 (95.9, 98.3) | 72.9 (69.6, 76.1) | 100.0 (99.5, 100.0) | 97.8 (96.5, 98.8) | 63.1 (59.5, 66.6)
18-64 | Td | 509 | 95.9 (93.8, 97.4) | 70.3 (66.2, 74.3) | 99.8 (98.9, 100.0) | 98.2 (96.7, 99.2) | 66.8 (62.5, 70.9)

Table 5: Pre-vaccination and Post-vaccination Antibody Responses and Booster Response Rates to Diphtheria Toxoid Following a First Vaccination with Adacel as Compared to Td Vaccine in Adolescents and Adults 11 through 64 Years of Age (Td506)
 |  |  | Anti-Diphtheria toxin (IU/mL) Pre-vaccination | Anti-Diphtheria toxin (IU/mL) Pre-vaccination | Anti-Diphtheria toxin (IU/mL) 1 Month Post-vaccination | Anti-Diphtheria toxin (IU/mL) 1 Month Post-vaccination | Anti-Diphtheria toxin (IU/mL) 1 Month Post-vaccination
Age Group (years) | Vaccine | N [N = number of participants in the per-protocol population with available data.] | % ≥0.10 (95% CI) | % ≥1.0 (95% CI) | % ≥0.10 (95% CI) | % ≥1.0 (95% CI) | % Booster [Booster response is defined as: A 4-fold rise in antibody concentration, if the pre-vaccination concentration was equal to or below the cut-off value and a 2-fold rise in antibody concentration if the pre-vaccination concentration was above the cut-off value. The cut-off value for diphtheria was 2.56 IU/mL.] (95% CI)
11-17 | Adacel | 527 | 72.5 (68.5, 76.3) | 15.7 (12.7, 19.1) | 99.8 [Seroprotection rates at ≥0.10 IU/mL and booster response rates to Adacel were non-inferior to Td vaccine (upper limit of the 95% CI on the difference for Td vaccine minus Adacel <10%).] (98.9, 100.0) | 98.7 [Seroprotection rates at ≥1.0 IU/mL were not prospectively defined as a primary endpoint.] (97.3, 99.5) | 95.1 (92.9, 96.8)
11-17 | Td [Tetanus and Diphtheria Toxoids Adsorbed manufactured by Sanofi Pasteur Inc., Swiftwater, PA.] | 515-516 | 70.7 (66.5, 74.6) | 17.3 (14.1, 20.8) | 99.8 (98.9, 100.0) | 98.4 (97.0, 99.3) | 95.0 (92.7, 96.7)
18-64 | Adacel | 739-741 | 62.6 (59.0, 66.1) | 14.3 (11.9, 17.0) | 94.1 (92.1, 95.7) | 78.0 (74.8, 80.9) | 87.4 (84.8, 89.7)
18-64 | Td | 506-507 | 63.3 (59.0, 67.5) | 16.0 (12.9, 19.5) | 95.1 (92.8, 96.8) | 79.9 (76.1, 83.3) | 83.4 (79.9, 86.5)

Table 6: Ratio of Pertussis Antibody Geometric Mean Concentrations (GMCs) [Antibody GMCs, measured in arbitrary ELISA units were calculated separately for infants, adolescents and adults.] Observed One Month Following a First Vaccination with Adacel in Adolescents and Adults 11 through 64 Years of Age Compared with Those Observed in Infants One Month Following Vaccination at 2,4 and 6 Months of Age in the Efficacy Trial with DAPTACEL (Sweden I Efficacy Study)
 | Adolescents 11-17 Years of Age Adacel [N = 524 to 526, number of adolescents in the per-protocol population with available data for Adacel.] /DAPTACEL [N = 80, number of infants who received DAPTACEL with available data post dose 3 (Sweden Efficacy I).] GMC Ratio (95% CIs) | Adults 18-64 Years of Age Adacel [N = 741, number of adults in the per-protocol population with available data for Adacel.] /DAPTACEL GMC Ratio (95% CIs)
 | Anti-PT | 3.6 (2.8, 4.5) [GMC following Adacel was non-inferior to GMC following DAPTACEL (lower limit of 95% CI on the ratio of GMC for Adacel divided by DAPTACEL >0.67).] | 2.1 (1.6, 2.7)
Anti-FHA | 5.4 (4.5, 6.5) | 4.8 (3.9, 5.9)
Anti-PRN | 3.2 (2.5, 4.1) | 3.2 (2.3, 4.4)
Anti-FIM | 5.3 (3.9, 7.1) | 2.5 (1.8, 3.5)

Table 7: Booster Response Rates to the Pertussis Antigens Observed One Month Following a First Vaccination with Adacel in Adolescents and Adults 11 through 64 Years of Age
 | Adolescents 11-17 Years of Age N [N = number of participants in the per-protocol population with available data.] | Adolescents 11-17 Years of Age % (95% CI) | Adults 18-64 Years of Age N | Adults 18-64 Years of Age % (95% CI) | Predefined Acceptable Rates [The acceptable response rate for each antigen was defined as the lower limit of the 95% CI for the rate being no more than 10% lower than the response rate observed in previous clinical trials.] % [A booster response for each antigen was defined as a 4-fold rise in antibody concentration if the pre-vaccination concentration was equal to or below the cut-off value and a 2-fold rise in antibody concentration if the pre-vaccination concentration was above the cut-off value. The cut-off values for pertussis antigens were established based on antibody data from both adolescents and adults in previous clinical trials. The cut-off values were 85 EU/mL for PT, 170 EU/mL for FHA, 115 EU/mL for PRN and 285 EU/mL for FIM.]
 | Anti-PT | 524 | 92.0 (89.3, 94.2) | 739 | 84.4 (81.6, 87.0) | 81.2
Anti-FHA | 526 | 85.6 (82.3, 88.4) | 739 | 82.7 (79.8, 85.3) | 77.6
Anti-PRN | 525 | 94.5 (92.2, 96.3) | 739 | 93.8 (91.8, 95.4) | 86.4
Anti-FIM | 526 | 94.9 (92.6, 96.6) | 739 | 85.9 (83.2, 88.4) | 82.4

Study NCT01311557 assessed the comparative immunogenicity of a first vaccination with Adacel administered to adolescents (10 to <11 years of age and 11 to <12 years of age) [See ADVERSE REACTIONS (6.1).] In this study non-inferiority was demonstrated for booster responses to tetanus and diphtheria toxoids, GMCs to the pertussis antigens (PT, FHA, PRN and FIM) and booster responses to the pertussis antigens PT, FHA and PRN. For FIM, non-inferiority was not demonstrated as the lower bound of the 95% CI of the difference in booster response rates (-5.96%) did not meet the predefined criterion (>-5% when the booster response in the older age group was >95%).

14.2 Immunological Evaluation in Adults, 18 through 64 Years of Age Following a Second Vaccination with Adacel

In study NCT01439165 [See ADVERSE REACTIONS (6.1).], subjects 18 to 64 years of age who had received a dose of Adacel 8-12 years previously, were randomized to receive a second dose of Adacel or Td vaccine (Tetanus and Diphtheria Toxoids Adsorbed manufactured by Sanofi Pasteur, Limited). Blood samples for immunogenicity analyses were obtained from participants pre-vaccination and approximately 28 days post-vaccination. The per-protocol analysis set was used for all immunogenicity analyses, and included 948 participants in the Adacel group and 317 participants in the Td control vaccine group. Of the study participants, 35% were male. Of subjects who reported a racial/ethnic demographic, 95% were Caucasian, 2% Black, 0.5% American Indian or Alaska native, 1% Asian and 1.5% were of mixed or other origin.

A tetanus antitoxoid level of ≥0.1 IU/mL, measured by the ELISA used in this study was considered protective. An anti-diphtheria anti-toxin level of ≥0.1 IU/mL was considered protective. Pre-vaccination and post-vaccination seroprotection rates and booster response rates are presented in Table 8.

Table 8: Pre-vaccination and Post-vaccination Seroprotection Rates and Booster Response Rates to Tetanus Toxoid and Diphtheria Toxoid Following a Second Vaccination with Adacel Compared to Td Vaccine in Persons 18 through 64 Years of Age, Per Protocol Analysis Set
 | Vaccine | N [N = number of participants in the per-protocol population with available data.] | Pre-vaccination ≥0.1 IU/mL (95% CI) | Pre-vaccination ≥1.0 IU/mL (95% CI) | 1 month post-vaccination ≥0.1 IU/mL (95% CI) [Seroprotection rates at ≥0.10 IU/mL for Adacel were non-inferior to Td for diphtheria toxin and tetanus toxoid (upper limit of the 95% CI on the difference for Td vaccine minus Adacel <10%).] | 1 month post-vaccination ≥1.0 IU/mL (95% CI) [Seroprotection rates at ≥1.0 IU/mL were not prospectively defined as a primary or secondary endpoint.] | 1 month post-vaccination %Booster [Booster response is defined as a minimum rise in antibody concentration from pre to post-vaccination. The minimum rise is at least 2 times if the pre-vaccination concentration is above the cutoff value, or at least 4 times if it is at or below the cutoff value. The cutoff values for to tetanus and diphtheria are 2.7 IU/mL and 2.56 IU/mL, respectively.] (95% CI)
 | Vaccine | N [N = number of participants in the per-protocol population with available data.] | Anti- Tetanus Toxoid (ELISA - IU/mL) | Adacel | 944-948 | 97.2 (96.0; 98.2) | 62.3 (59.1; 65.4) | 100.0 (99.6; 100.0) | 99.9 (99.4; 100.0) | 74.5 [n/M: defines the number n of participants with booster response / the number M of subjects with available data to evaluate booster response. There were (n/M) 703/944, 257/315, 786/945 and 265/315 for Adacel/Tetanus, Td Adsorbed/Tetanus, Adacel/Diphtheria, and Td Adsorbed/Diphtheria, respectively.] [Booster response rates for tetanus toxoid in Adacel did not meet the pre-specified non-inferiority criteria.] (71.6; 77.2)
Anti- Tetanus Toxoid (ELISA - IU/mL) | Td [Tetanus and Diphtheria Toxoids Adsorbed manufactured by Sanofi Pasteur Limited, Toronto, Ontario, Canada.] Adsorbed | 315-317 | 96.5 (93.8; 98.2) | 63.8 (58.2; 69.1) | 100.0 (98.8; 100.0) | 100.0 (98.8; 100.0) | 81.6 (76.9; 85.7)
Anti- Diphtheria Toxin (ELISA - IU/mL) | Adacel | 945-948 | 84.7 (82.2; 86.9) | 29.1 (26.2; 32.1) | 99.8 (99.2; 100.0) | 94.9 (93.3; 96.2) | 83.2 (80.6; 85.5)
Anti- Diphtheria Toxin (ELISA - IU/mL) | Td Adsorbed | 315-317 | 83.8 (79.3; 87.7) | 29.8 (24.8; 35.2) | 99.4 (97.7; 99.9) | 94.0 (90.8; 96.4) | 84.1 (79.6; 88.0)

For all pertussis antigens (PT, FHA, PRN and FIM), post-vaccination anti-pertussis GMCs in the Adacel group were non-inferior to GMCs induced by 3 or 4 doses of DAPTACEL in historical studies as are presented in Table 9.

Table 9: Ratio of Pertussis Antibody Geometric Mean Concentrations (GMCs) Observed One Month Following a Second Vaccination with Adacel in Adults Compared with Those Observed in Infants One Month following Vaccination with 3 or 4 Doses of DAPTACEL (Per-Protocol Analysis Set)
Antigen | N | Adacel GMC (EU/mL) | Adacel (95% CI) | N | DAPTACEL [DAPTACEL: Historical controls who received DAPTACEL in Sanofi Pasteur studies. PT antibody GMC were compared to GMC following 4 doses of DAPTACEL in NCT00255047. FHA, PRN and FIM antibody GMCs were compared to GMCs following 3 doses of Daptacel in the Sweden I Efficacy trial.] GMC (EU/mL) | DAPTACEL (95% CI) | Adacel/DAPTACEL GMC Ratio | (95% CI) [For each pertussis antigen, non-inferiority was demonstrated if the lower limit of the 2-sided 95% CI of the GMC ratio (Adacel divided by the historical control) was > 0.66.]
Antigen | PT | 935 | 102 | (94.9; 110) | 366 | 98.1 | (90.9; 106) | 1.04 | (0.92; 1.18)
FHA | 948 | 209 | (200; 217) | 80 | 39.9 | (34.6; 46.1) | 5.22 | (4.51; 6.05)
PRN | 948 | 318 | (302; 334) | 80 | 108 | (91.4; 128) | 2.94 | (2.46; 3.51)
FIM | 948 | 745 | (711; 781) | 80 | 341 | (270; 431) | 2.18 | (1.84; 2.60)

Booster response rates for PT and FHA were non-inferior in Adacel participants compared to pre-specified criteria for booster response rates, but non-inferiority was not achieved for PRN and FIM booster response rates (See Table 10).

Table 10: Comparison of Booster Response [Booster response is defined as a minimum rise in antibody concentration from pre to post-vaccination. The minimum rise is at least 2-fold if the pre-vaccination concentration is above the cutoff value, or at least 4-fold if it is at or below the cutoff value. The cutoff values for Study NCT01439165 for the pertussis antigens are: 93 EU/mL for PT, 170 EU/mL for FHA, 115 EU/mL for PRN, and 285 EU/mL for FIM.] Rates for Pertussis Antigens Following a Second Vaccination with Adacel (Per-Protocol Analysis Set)
 | Adacel (N=948) | Adacel (N=948) | Pre-specified criteria for Booster Response Rates [Pre-specified criteria for booster response rates were derived from participants 21 to <65 years of age who received Adacel in Study Td506.] | Adacel minus Pre-specified Booster Response Rates | Adacel minus Pre-specified Booster Response Rates
Antigen | n/M | % (95% CI) | % | Difference (%) | (95% CI) [Non-inferiority in booster response rate for each pertussis antigen was demonstrated if the lower limit of the 2-sided 95% CI of the difference of booster response rates between participants receiving Adacel in Study NCT01439165 and expected booster response rates based on Study Td506 was >-10%.]
PT | 693/894 | 77.5 (74.6; 80.2) | 61.4 | 16.12 | (13.27; 18.73)
FHA | 651/945 | 68.9 (65.8; 71.8) | 73.1 | -4.21 | (-7.23; -1.34)
PRN | 617/945 | 65.3 (62.2; 68.3) | 83.9 | -18.61 | (-21.7; -15.6)
FIM | 537/945 | 56.8 (53.6; 60.0) | 75.9 | -19.07 | (-22.3; -16.0)
N = number of subjects analyzed according to Per-Protocol Analysis Set
M = number of subjects with available data for the considered endpoint
n = number of subjects fulfilling the item listed in the first column

14.3 Study in Pregnant Women

The effectiveness of Adacel immunization during the third trimester of pregnancy to prevent pertussis among infants younger than 2 months of age was assessed based on a re-analysis of the Adacel-relevant data (Study NCT05040802) from an observational study of Tdap vaccine effectiveness in the United States (9). This matched case-control study included pertussis cases reported from 2011 through 2014 in infants born at ≥ 37 weeks gestation and ≥ 2 days old. A case of pertussis was defined as the onset of cough illness and at least one of the following: laboratory-confirmation (culture or PCR) of pertussis, epidemiological linkage to a laboratory-confirmed case, or clinically-compatible illness (cough ≥2 weeks with paroxysms, inspiratory whoop or post-tussive vomiting) in an infant <2 months old. NCT05040802 included a total of 596 infants (179 cases of pertussis and 417 controls without pertussis), the mean age was 4.2 (SD, 2.5) weeks, and 45.7% were non-Hispanic. For the vaccine effectiveness re-analysis, a conditional logistic regression model controlling for infant's age and maternal education, was fit to data from 101 cases (including 5 infants whose mothers received Adacel during the third trimester and ≥14 days before delivery) and 171 controls (including 27 infants whose mothers received Adacel during the third trimester and ≥14 days before delivery) matched by birth hospital. This resulted in a vaccine effectiveness estimate of 88.0% (95% CI: 43.8, 97.4) for vaccination during the third trimester and ≥14 days before delivery.

14.4 Immune Responses to Pertussis Vaccination in Infants Born to Mothers Who Received Adacel During Pregnancy

Published studies have reported diminished immune responses to pertussis antigens in DTaP-containing vaccines administered to infants whose mothers received Adacel during the third trimester of pregnancy compared with infants whose mothers did not receive Adacel during the third trimester of pregnancy (10, 11). Whether the diminished immune responses observed in vaccinated infants whose mothers received Adacel during pregnancy result in diminished effectiveness of pertussis vaccination in infants is unknown.

14.5 Concomitant Hepatitis B Vaccine Administration

The concomitant use of Adacel (first vaccination) and hepatitis B (Hep B) vaccine (Recombivax HB®, 10 mcg per dose using a two-dose regimen, manufactured by Merck and Co., Inc.) was evaluated in a multi-center, open-labeled, randomized, controlled study that enrolled 410 adolescents, 11 through 14 years of age inclusive. One group received Adacel and Hep B vaccines concurrently (N = 206). The other group (N = 204) received Adacel at the first visit, then 4-6 weeks later received Hep B vaccine. The second dose of Hep B vaccine was given 4-6 weeks after the first dose. Serum samples were obtained prior to and 4-6 weeks after Adacel administration, as well as 4-6 weeks after the 2nd dose of Hep B for all participants. No interference was observed in the immune responses to any of the vaccine antigens when Adacel and Hep B vaccines were given concurrently or separately. [See ADVERSE REACTIONS (6.1).]

14.6 Concomitant Influenza Vaccine Administration

The concomitant use of Adacel (first vaccination) and trivalent inactivated influenza vaccine (TIV, Fluzone®, manufactured by Sanofi Pasteur Inc., Swiftwater, PA) was evaluated in a multi-center, open-labeled, randomized, controlled study conducted in 720 adults, 19-64 years of age inclusive. In one group, participants received Adacel and TIV vaccines concurrently (N = 359). The other group received TIV at the first visit, then 4-6 weeks later received Adacel (N = 361). Sera were obtained prior to and 4-6 weeks after Adacel, as well as 4-6 weeks after the TIV. The immune responses were comparable for concurrent and separate administration of Adacel and TIV vaccines for diphtheria (percent of participants with seroprotective concentration ≥0.10 IU/mL and booster responses), tetanus (percent of participants with seroprotective concentration ≥0.10 IU/mL), pertussis antigens (booster responses and GMCs except lower PRN GMC in the concomitant group, lower bound of the 90% CI was 0.61 and the prespecified criterion was ≥0.67) and influenza antigens (percent of participants with hemagglutination-inhibition [HI] antibody titer ≥1:40 IU/mL and ≥4-fold rise in HI titer). Although tetanus booster response rates were significantly lower in the group receiving the vaccines concurrently versus separately, greater than 98% of participants in both groups achieved seroprotective levels of ≥0.1 IU/mL. [See ADVERSE REACTIONS (6.1).]

15 REFERENCES

1 Stratton KR, et al, editors. Adverse events associated with childhood vaccines; evidence bearing on causality. Washington: National Academy Press; 1994. p. 67-117.
2 Stainer DW, et al. A simple chemically defined medium for the production of phase I Bordetella pertussis. J Gen Microbiol 1970;63:211-20.
3 Mueller JH, et al. Variable factors influencing the production of tetanus toxin. J Bacteriol 1954;67(3):271-7.
4 Stainer DW. Production of diphtheria toxin. In: Manclark CR, editor. Proceedings of an informal consultation on the World Health Organization requirements for diphtheria, tetanus, pertussis and combined vaccines. United States Public Health Service, Bethesda, MD. DHHS 91-1174. 1991. p. 7-11.
5 FDA. Department of Health and Human Services (DHHS). Biological products bacterial vaccines and toxoids; implementation of efficacy review; proposed rule. Fed Reg 1985;50(240):51002-117.
6 Wassilak SGF, et al. Tetanus toxoid. In: Plotkin SA, Orenstein WA, Offit PA, editors. Vaccines. 5th ed. Philadelphia, PA: WB Saunders Company; 2008. p. 805-39.
7 Vitek CR and Wharton M. Diphtheria toxoid. In: Plotkin SA, Orenstein WA, Offit PA, editors. Vaccines. 5th ed. Philadelphia, PA: W.B. Saunders Company; 2008. p. 139-56.
8 Gustafsson L, et al. A controlled trial of a two-component acellular, a five-component acellular and a whole-cell pertussis vaccine. N Engl J Med 1996;334(6):349-55.
9 Skoff TH, Kenyon C, Cocoros N, Liko J, Miller L, Kudish K, et al. Sources of infant pertussis infection in the United States. Pediatrics. 2015;136(4):635-41.
10 Halperin, SA et al. A randomized controlled trial of the safety and immunogenicity of tetanus, diphtheria, and acellular pertussis vaccine immunization during pregnancy and subsequent infant immune response. Clin Infect Dis. 2018;67(7):1063-71.
11 Munoz, FM et al. Safety and immunogenicity of tetanus diphtheria and acellular pertussis (Tdap) immunization during pregnancy in mothers and infants: a randomized clinical trial. JAMA. 2014;311(17):1760-9.

16 HOW SUPPLIED/STORAGE AND HANDLING

Syringe, without needle, single-dose – NDC 49281-400-89 (not made with natural rubber latex); in package of 5 syringes, NDC 49281-400-20.

Vial, single-dose – NDC 49281-400-58; in package of 5 vials; NDC 49281-400-05. The vial stopper is not made with natural rubber latex. Discard unused portion in vial.

Vial, single-dose – NDC 49281-400-58; in package of 10 vials; NDC 49281-400-10. The vial stopper is not made with natural rubber latex. Discard unused portion in vial.

Not all pack sizes may be marketed.

STORAGE AND HANDLING

Adacel should be stored at 2°C to 8°C (35°F to 46°F). DO NOT FREEZE. Product which has been exposed to freezing should not be used. Do not use after expiration date shown on the label.

17 PATIENT COUNSELING INFORMATION

Before administration of Adacel, healthcare providers should inform the patient, parent or guardian of the benefits and risks of the vaccine and the importance of receiving recommended booster dose unless a contraindication to further immunization exists.

The healthcare provider should inform the patient, parent or guardian about the potential for adverse reactions that have been temporally associated with Adacel or other vaccines containing similar components. The healthcare provider should provide the Vaccine Information Statements (VISs) that are required by the National Childhood Vaccine Injury Act of 1986 to be given with each immunization. The patient, parent or guardian should be instructed to report any serious adverse reactions to their healthcare provider.

Pregnancy Exposure Registry

[See USE IN SPECIFIC POPULATIONS (8.1).]

Manufactured by:
Sanofi Pasteur Limited
Toronto Ontario Canada

Distributed by:
Sanofi Pasteur Inc.
Swiftwater PA 18370 USA

Adacel® is a registered trademark of Sanofi, its affiliates, and its subsidiaries.

© 2024, Sanofi Pasteur Inc - All rights reserved

R17-0624 USA

Patient Information Sheet Adacel® Tetanus Toxoid, Reduced Diphtheria Toxoid and Acellular Pertussis Vaccine Adsorbed

Please read this information before vaccination with Adacel vaccine. This summary is not intended to take the place of talking with your healthcare provider. If you have questions or would like more information, please talk with your healthcare provider.

What is Adacel vaccine?

Adacel vaccine is a vaccine that helps protect against tetanus, diphtheria, and pertussis diseases in people who are 10 through 64 years of age. It cannot cause tetanus, diphtheria, or pertussis. Adacel vaccine may not protect all people getting the vaccine.

Adacel given during the third trimester of pregnancy helps the pregnant woman create antibodies against the bacteria that cause whooping cough (pertussis) that are passed to her baby before birth. These antibodies help protect the baby against whooping cough during the first few months of life.

Tetanus, also called "lockjaw", can cause severe muscle spasms making it difficult for a person to open their mouth or swallow. You can get tetanus through a cut or wound.

Diphtheria can cause throat, lung and skin infections leading to severe complications that affect the lungs, heart and nervous system.

Pertussis, also called "whooping cough," causes coughing fits that can affect breathing. Diphtheria and pertussis are spread from person to person.

Who should not get Adacel vaccine?

You should not get Adacel vaccine if you:

- had a severe allergic reaction to a previous tetanus vaccine, diphtheria vaccine, pertussis vaccine, or any component of Adacel vaccine.
- were told you have an "encephalopathy", which is a kind of brain disease or malfunction, after receiving a previous dose of a pertussis vaccine.
- are younger than 10 years old or older than 64 years of age.

What should I tell my healthcare provider before I or my child gets Adacel vaccine?

Tell your healthcare provider if you or your child:

- had severe injection site pain or swelling after a prior tetanus, diphtheria, or pertussis vaccination.
- had Guillain-Barré syndrome, a nerve disease causing severe muscle weakness, after getting a vaccine.
- have a brain disorder or brain disease that is not stable.
- are pregnant or nursing.
- had a tetanus, diphtheria, or pertussis vaccine within the last 5 years.

Fainting can occur around the time of vaccination with Adacel or other vaccines. Tell your healthcare provider if you or your child has fainted in connection with any previous vaccination.

How is Adacel vaccine given?

Adacel is a single shot that is given into the muscle of the upper arm.

What are the possible side effects of Adacel vaccine?

The most common side effects of Adacel vaccine are:

- pain, redness and swelling where you got the shot
- headache
- body ache
- tiredness
- fever

These are not all the possible side effects of Adacel vaccine. You may ask your healthcare provider for a list of side effects that is available to healthcare professionals.

If you or your child experience side effects that concern you, call your healthcare provider for medical advice. You may report side effects to VAERS at 1-800-822-7967 or http://vaers.hhs.gov.

What ingredients are in Adacel vaccine?

Adacel vaccine contains noninfectious tetanus, diphtheria, and pertussis proteins, aluminum phosphate, 2-phenoxyethanol, and residual amounts of formaldehyde and glutaraldehyde.

Adacel vaccine does not contain preservatives.

Manufactured by:
Sanofi Pasteur Limited
Toronto Ontario Canada

Distributed by:
Sanofi Pasteur Inc.
Swiftwater PA 18370 USA

R13-1220 USA

PRINCIPAL DISPLAY PANEL - 0.5 mL Vial Label

Adolescent/Adult
Tdap

NDC 49281-400-58
Tetanus Toxoid, Reduced
Diphtheria Toxoid and
Acellular Pertussis
Vaccine Adsorbed

Adacel®

Rx only

Single-dose (0.5 mL) IM only

Sanofi Pasteur Limited

PRINCIPAL DISPLAY PANEL - 0.5 mL Vial Package

NDC 49281-400-10
Tdap

Tetanus Toxoid,
Reduced Diphtheria
Toxoid and Acellular
Pertussis Vaccine
Adsorbed

10 single-dose vials

Rx only

Adacel®

For adolescent and adult use.

SANOFI PASTEUR

PRINCIPAL DISPLAY PANEL - 0.5 mL Syringe Label

Single-dose (0.5 mL)
IM only
Tdap

Tetanus Toxoid, Reduced
Diphtheria Toxoid and Acellular
Pertussis Vaccine Adsorbed

Adacel®

Adolescent/Adult

Rx only

Sanofi Pasteur Limited

PRINCIPAL DISPLAY PANEL - 0.5 mL Syringe Package

NDC 49281-400-20
Tdap

Tetanus Toxoid, Reduced
Diphtheria Toxoid
and Acellular
Pertussis Vaccine
Adsorbed

5 single-dose
prefilled syringes
0.5 mL each

Rx only

Adacel®

For adolescent and adult use.

SANOFI PASTEUR